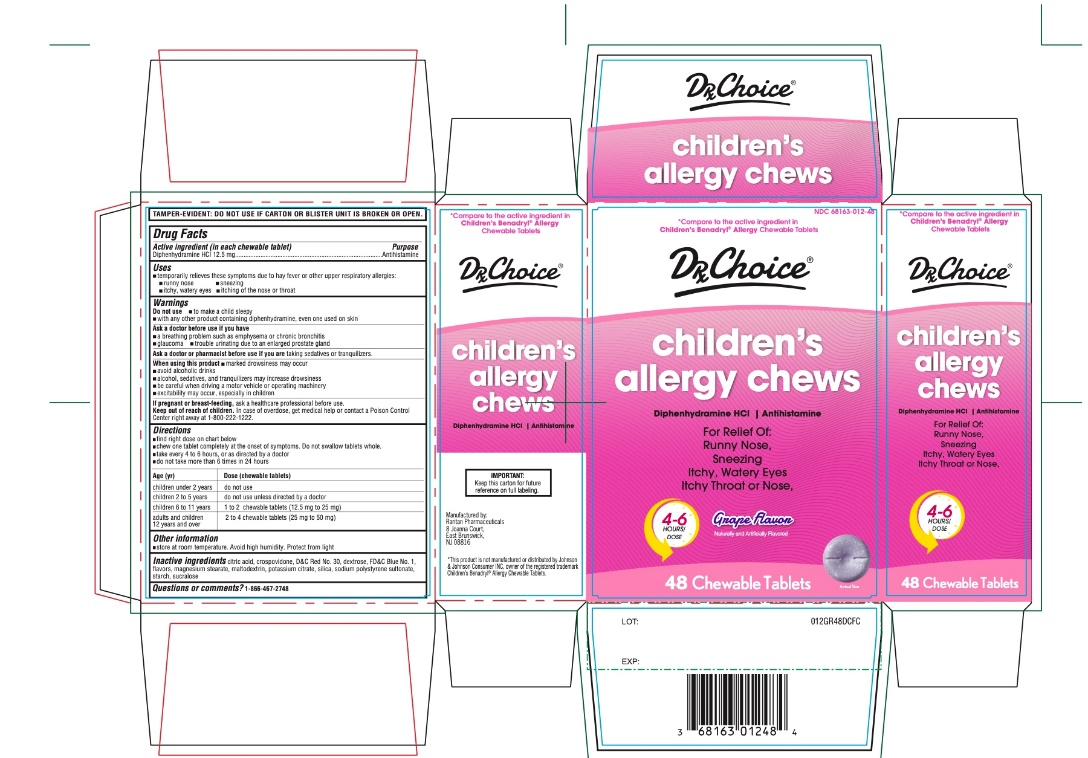 DRUG LABEL: Drx Choice childrens allergy chews
NDC: 68163-012 | Form: TABLET, CHEWABLE
Manufacturer: RARITAN PHARMACEUTICALS INC
Category: otc | Type: HUMAN OTC DRUG LABEL
Date: 20250930

ACTIVE INGREDIENTS: DIPHENHYDRAMINE HYDROCHLORIDE 12.5 mg/1 1
INACTIVE INGREDIENTS: CITRIC ACID MONOHYDRATE; CROSPOVIDONE (120 .MU.M); D&C RED NO. 30; DEXTROSE, UNSPECIFIED FORM; FD&C BLUE NO. 1; MAGNESIUM STEARATE; MALTODEXTRIN; POTASSIUM CITRATE; SILICON DIOXIDE; SODIUM POLYSTYRENE SULFONATE; STARCH, CORN; SUCRALOSE

DRx Choice children’s allergy chews

Active ingredient (in each tablet)

Diphenhydramine HCl 12.5 mg

Purpose

Antihistamine

Uses

- temporarily relieves these symptoms due to hay fever or other upper respiratory allergies.
  - runny nose
  - itchy, watery eyes
  - sneezing
  - itching of the nose or throat

Warnings

Do not use

- to make a child sleepy
- with any other product containing diphenhydramine, even one used on skin

Ask your doctor before use if you have

- glaucoma
- a breathing problem such as emphysema or chronic bronchitis
- trouble urinating due to an enlarged prostate gland

Ask a doctor or pharmacist before use if you are

taking sedatives or tranquilizers.

When using this product

- marked drowsiness may occur
- avoid alcoholic drinks
- alcohol, sedatives, and tranquilizers may increase drowsiness
- be careful when driving a motor vehicle or operating machinery
- excitability may occur, especially in children

If pregnant or breast-feeding,

ask a health professional before use.

Keep out of reach of children.

In case of overdose, get medical help or contact a Poison Control Center right away at 1-800-222-1222

Directions

- chew one tablet completely at the onset of symptoms. Do not swallow tablets whole.
- Find right dose on chart below
- take every 4 to 6 hours, or as directed by a doctor
- do not take more than 6 doses in 24 hours

Age (Yr) | Dose (chewable tablets)
children under 2 years of age | do not use
children 2 to under 5 years of age | do not use unless directed by a doctor
children 6 to under 12 years of age | 1 to 2 tablets
adults and children 12 years of age and over | 2 to 4 tablets

Other information

- store below at room temperature. Avoid high humidity. Protect from light.

Inactive ingredients

citric acid, crospovidone, D&C Red No.30, dextrose, FD&C Blue No 1, flavors, magnesium stearate, maltodextrin, potassium citrate, silica, sodium polystyrene sulfonate, starch, sucralose

Questions or comments ?

1-866-467-2748

Principal Display Panel

NDC 68163-012-48

Compare to active ingredient in Children's Benadryl® Allergy Chewable Tablets

DRx Choice

children's allergy chews
diphenhydramine HCl, 12.5 mg/ antihistamine

For Relief of:

- Sneezing
- Runny nose
- Itchy throat or Nose
- Itchy, watery eyes

48 Chewable Tablets

Grape Flavor

4-6 HOURS/DOSE

TAMPER EVIDENT: DO NOT USE IF CARTON IS OPENED OR IF BLISTER UNIT IS TORN, BROKEN OR SHOWS ANY SIGNS OF TAMPERING

*This product is not manufactured or distributed by Johnson & Johnson Consumer INC, owner of the registered trademark Children's Benadryl® Allergy Chewable Tablets.

Manufactured by:

Raritan Pharmaceuticals

8 Joanna Court,

East Brunswick,

NJ 08816

IMPORTANT:Keep this carton for future reference on full labelling